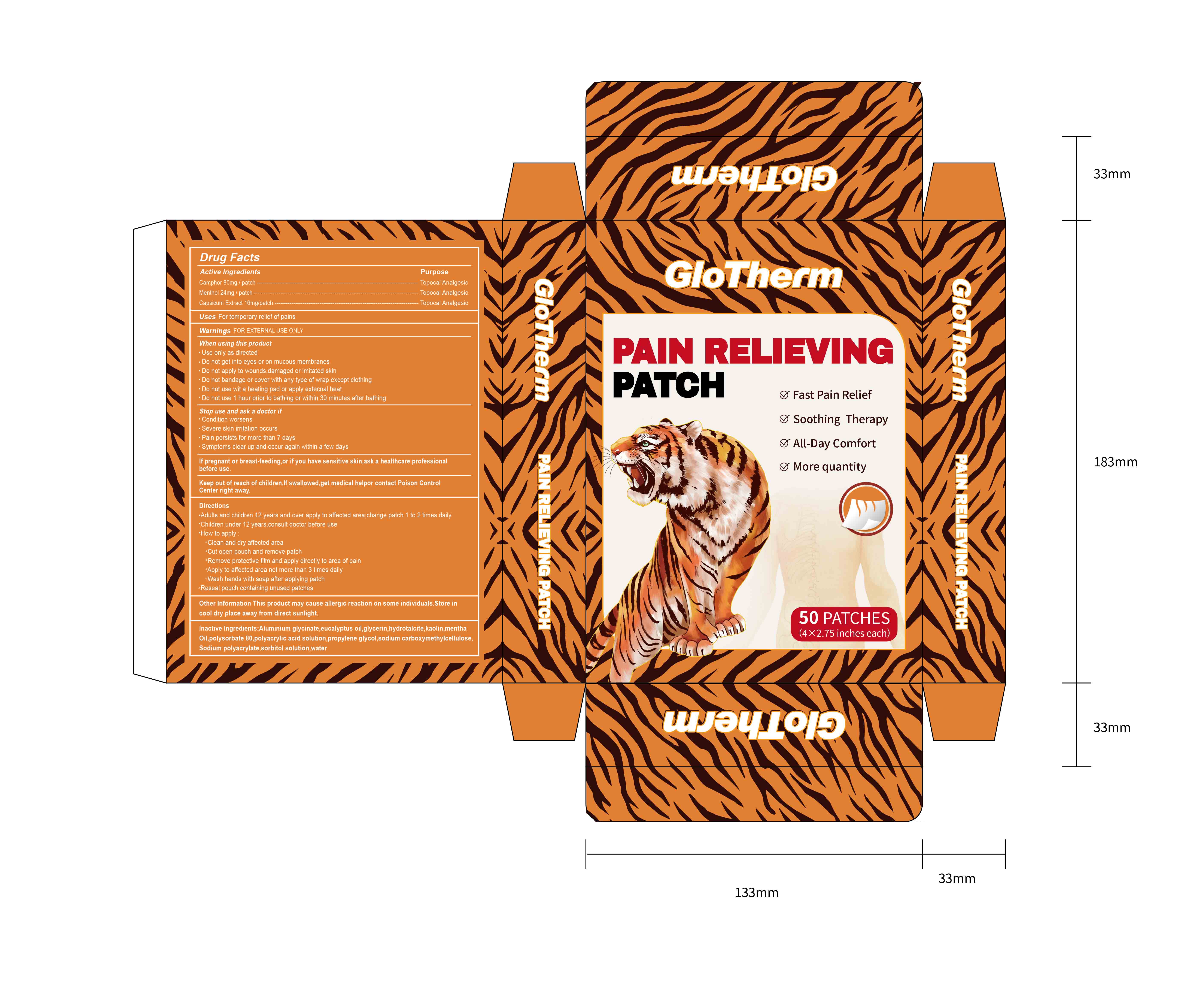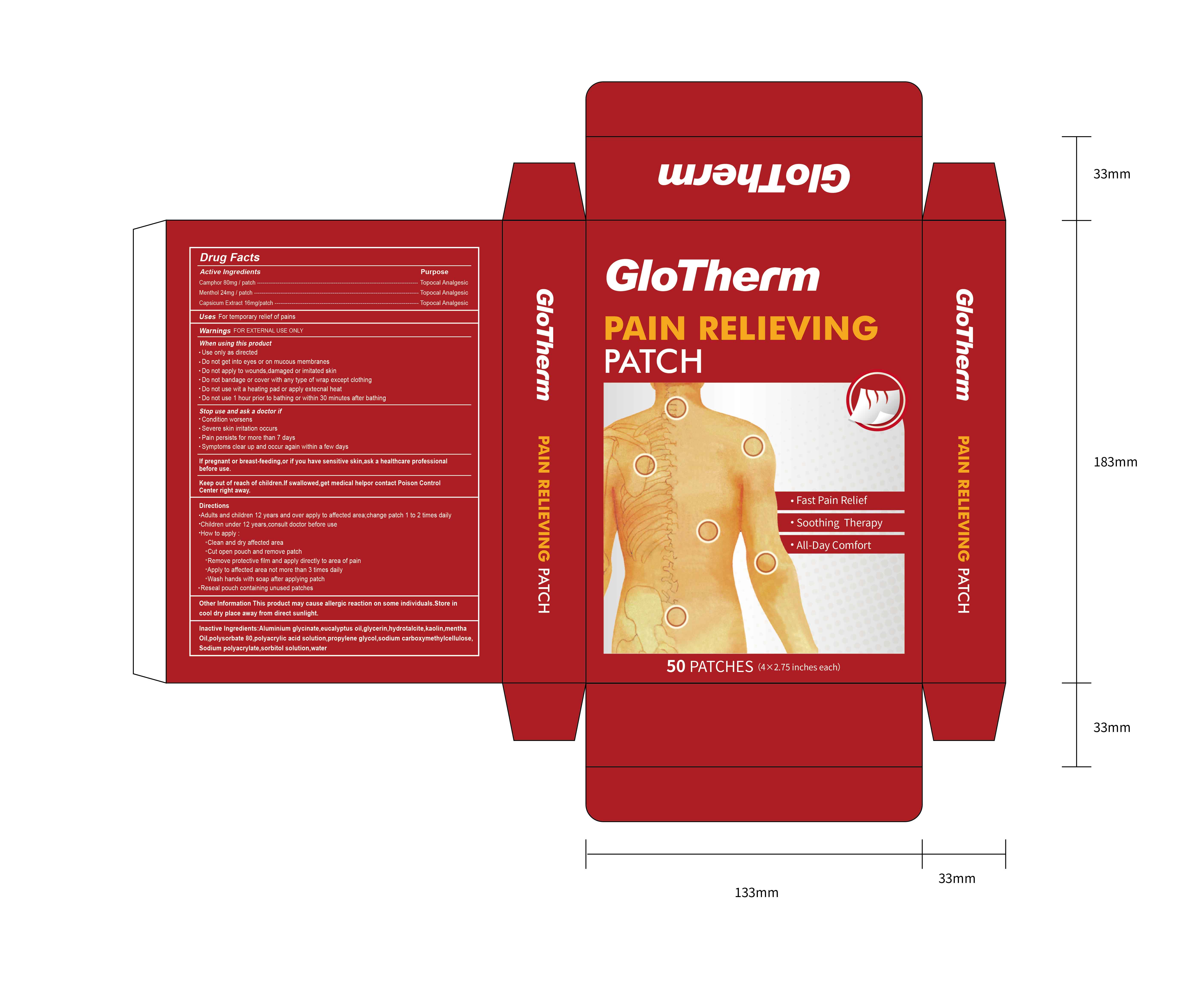 DRUG LABEL: PAIN RELIEVING
NDC: 85009-001 | Form: PATCH
Manufacturer: Changsha Yunhan Hechuang E-Commerce Co., Ltd.
Category: otc | Type: HUMAN OTC DRUG LABEL
Date: 20241203

ACTIVE INGREDIENTS: MENTHOL 24 mg/100 1; CAMPHOR (NATURAL) 80 mg/100 1; CAPSICUM 16 mg/100 1
INACTIVE INGREDIENTS: PEPPERMINT OIL; EUCALYPTUS OIL; SORBITOL SOLUTION; GLYCERIN; POLYSORBATE 80; CARBOXYMETHYLCELLULOSE SODIUM; KAOLIN; DIHYDROXYALUMINUM AMINOACETATE; PROPYLENE GLYCOL; SODIUM POLYACRYLATE (2500000 MW); WATER; CARBOMER; HYDROTALCITE

85009-001

ACTIVE INGREDIENT

Camphor 80mg/patch

Menthol 24mg/patch

Capsicum Extract 16mg/patch

PURPOSE

Topocal Analgesic

Uses

For temporary relief of pains

Warnings FOR EXTERNAL USE ONLY

· Do not use wit a heating pad or apply extecnal heat

· Do not use 1 hour prior to bathing or within 30 minutes after bathing

When using this product

· Use only as directed

· Do not get into eyes or on mucous membranes

· Do not apply to wounds,damaged or imitated skin

· Do not bandage or cover with any type of wrap except clothing

· Do not use wit a heating pad or apply extecnal heat

· Do not use 1 hour prior to bathing or within 30 minutes after bathing

Stop use and ask a doctor if

· Condition worsens

· Severe skin irritation occurs

· Pain persists for more than 7 days

· Symptoms clear up and occur again within a few days

If pregnant or breast-feeding,or if you have sensitive skin,ask a healthcare professional before use.

Keep out of reach of children.lf swallowed,get medical helpor contact Poison Control Center right away.

Directions

· Adults and children 12 years and over apply to affected area;change patch 1 to 2 times daily

· Children under 12 years,consult doctor before use

· How to apply:

· Clean and dry affected area

· Cut open pouch and remove patch

· Remove protective film and apply directly to area of pain

· Apply to affected area not more than 3 times daily

· Wash hands with soap after applying patch · Reseal pouch containing unused patches

Other Information This product may cause allergic reaction on some individuals.Store in cool dry place away from direct sunlight.

INACTIVE INGREDIENT

Inactive Ingredients:Aluminium glycinate,eucalyptus oil,glycerin,hydrotalcite,kaolin,mentha oil,polysorbate 80,polyacrylic acid solution,propylene glycol,sodium carboxymethylcellulose,sodium polyacrylate,sorbitol solution,water